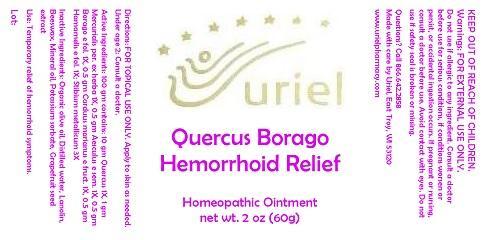 DRUG LABEL: Quercus Borago Hemorrhoid Relief
NDC: 48951-8116 | Form: OINTMENT
Manufacturer: Uriel Pharmacy Inc.
Category: homeopathic | Type: HUMAN OTC DRUG LABEL
Date: 20140612

ACTIVE INGREDIENTS: QUERCUS ROBUR WHOLE 1 [hp_X]/1 g; MERCURIALIS PERENNIS 1 [hp_X]/1 g; HORSE CHESTNUT 1 [hp_X]/1 g; BORAGE 1 [hp_X]/1 g; MILK THISTLE 1 [hp_X]/1 g; HAMAMELIS VIRGINIANA ROOT BARK/STEM BARK 1 [hp_X]/1 g; ANTIMONY 3 [hp_X]/1 g
INACTIVE INGREDIENTS: OLIVE OIL; WATER; LANOLIN; YELLOW WAX; MINERAL OIL; POTASSIUM SORBATE; CITRUS PARADISI SEED

Quercus Borago Hemorrhoid Relief

INDICATIONS AND USAGE

Directions: FOR TOPICAL USE ONLY.

DOSAGE AND ADMINISTRATION

Apply to skin as needed. Under age 2: Consult a doctor.

ACTIVE INGREDIENT

Active Ingredients: 100 gm contains: 10 gm Quercus 1X, 1 gm Mercurialis per. ex herba 1X, 0.5 gm Aesculus e sem. 1X, 0.5 gm Borago e fol. 1X, 0.5 gm Carduus marianus e fruct. 1X, 0.5 gm Hamamelis e fol. 1X; Stibium metallicum 3X

INACTIVE INGREDIENT

Inactive Ingredients: Organic olive oil, Distilled water, Lanolin, Beeswax, Mineral oil, Potassium sorbate, Grapefruit seed extract

PURPOSE

Use: Temporary relief of hemorrhoid symptoms.

KEEP OUT OF REACH OF CHILDREN.

WARNINGS

Warnings: FOR EXTERNAL USE ONLY. Do not use if allergic to any ingredient. Consult a doctor before use for serious conditions, if conditions worsen or persist, or accidental ingestion occurs. If pregnant or nursing, consult a doctor before use. Avoid contact with eyes. Do not use if safety seal is broken or missing.

QUESTIONS

Questions? Call 866.642.2858 Made with care by Uriel, East Troy, WI 53120 www.urielpharmacy.com